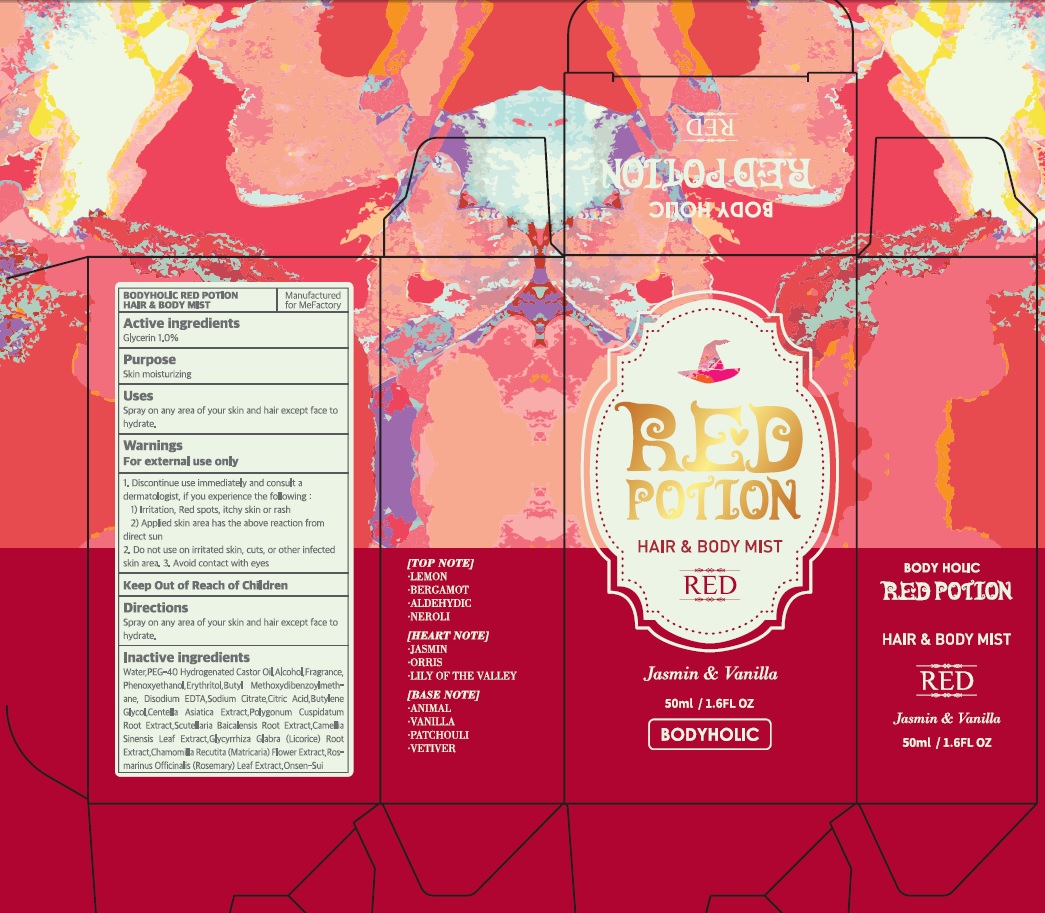 DRUG LABEL: BODYHOLIC RED POTION HAIR AND BODY MIST
NDC: 70908-110 | Form: SPRAY
Manufacturer: MeFactory Co., Ltd.
Category: otc | Type: HUMAN OTC DRUG LABEL
Date: 20170413

ACTIVE INGREDIENTS: Glycerin 0.5 g/50 mL
INACTIVE INGREDIENTS: Water; Alcohol

ACTIVE INGREDIENT

Active ingredients: Glycerin 1.0%

INACTIVE INGREDIENT

Inactive ingredients: Water, PEG-40 Hydrogenated Castor Oil, Alcohol, Fragrance, Phenoxyethanol, Erythritol, Butyl Methoxydibenzoylmethane, Disodium EDTA, Sodium Citrate, Citric Acid, Butylene Glycol, Centella Asiatica Extract, Polygonum Cuspidatum Root Extract, Scutellaria Baicalensis Root Extract, Camellia Sinensis Leaf Extract, Glycyrrhiza Glabra (Licorice) Root Extract, Chamomilla Recutita (Matricaria) Flower Extract, Rosmarinus Officinalis (Rosemary) Leaf Extract, Onsen-Sui

PURPOSE

Purpose: Skin moisturizing

WARNINGS

Warnings: For external use only 1. Discontinue use immediately and consult a dermatologist, if you experience the following: 1) Irritation, Red spots, itchy skin or rash 2) Applied skin area has the above reaction from direct sun 2. Do not use on irritated skin, cuts, or other infected skin area. 3. Avoid contact with eyes

KEEP OUT OF REACH OF CHILDREN

Uses

Uses: Spray on any area of your skin and hair except face to hydrate.

Directions

Directions: Spray on any area of your skin and hair except face to hydrate.